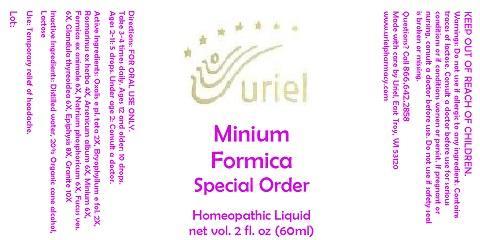 DRUG LABEL: Minimum Formica Special Order
NDC: 48951-7057 | Form: LIQUID
Manufacturer: Uriel Pharmacy Inc.
Category: homeopathic | Type: HUMAN OTC DRUG LABEL
Date: 20140929

ACTIVE INGREDIENTS: FORMICA RUFA 6 [hp_X]/1 mL; SODIUM PHOSPHATE, DIBASIC, HEPTAHYDRATE 6 [hp_X]/1 mL; FUCUS VESICULOSUS 6 [hp_X]/1 mL; THYROID, UNSPECIFIED 6 [hp_X]/1 mL; BOS TAURUS PINEAL GLAND 8 [hp_X]/1 mL; PENOXSULAM 10 [hp_X]/1 mL
INACTIVE INGREDIENTS: WATER; ALCOHOL; LACTOSE

Minimum Formica Special Order

INDICATIONS AND USAGE

Directions: FOR ORAL USE ONLY.

DOSAGE AND ADMINISTRATION

Take 3-4 times daily. Ages 12 and older: 10 drops. Ages 2-11: 5 drops. Under age 2: Consult a doctor.

ACTIVE INGREDIENT

Active Ingredients: Oxalis e pl. tota 2X, Bryophyllum e fol. 2X, Rosmarinus ex herba 4X, Arsenicum album 6X, Minium 6X, Formica ex animale 6X, Natrium phosphoricum 6X, Fucus ves. 6X, Glandula thyreoidea 6X, Epiphysis 8X, Granite 10X

INACTIVE INGREDIENT

Inactive Ingredients: Distilled water, 20% Organic cane alcohol, Lactose

PURPOSE

Use: Temporary relief of headache.

KEEP OUT OF REACH OF CHILDREN.

WARNINGS

Warnings: Do not use if allergic to any ingredient. Contains traces of lactose. Consult a doctor before use for serious conditions or if conditions worsen or persist. If pregnant or nursing, consult a doctor before use. Do not use if safety seal is broken or missing.

QUESTIONS

Questions? Call 866.642.2858 Made with care by Uriel, East Troy, WI 53120 www.urielpharmacy.com